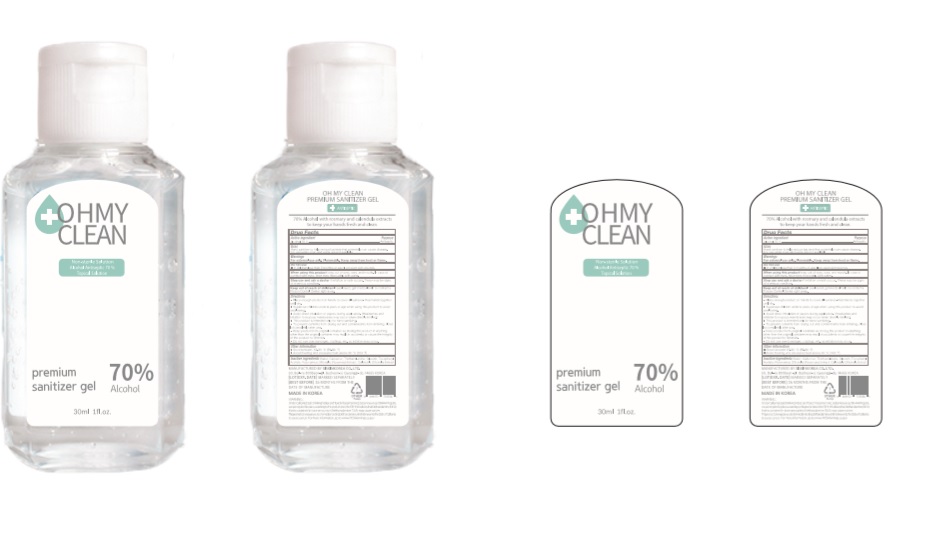 DRUG LABEL: OHMYCLEAN Premium sanitizer gel
NDC: 74514-0037 | Form: GEL
Manufacturer: SISKINKOREA CO.,LTD.
Category: otc | Type: HUMAN OTC DRUG LABEL
Date: 20200424

ACTIVE INGREDIENTS: ALCOHOL 21 mL/30 mL
INACTIVE INGREDIENTS: TROLAMINE; GLYCERIN; .ALPHA.-TOCOPHEROL ACETATE; CALENDULA OFFICINALIS WHOLE; WATER; ROSEMARY; CARBOMER HOMOPOLYMER, UNSPECIFIED TYPE

30ml_70%_gel_OHMYCLEAN Premium sanitizer gel [74514-0037-1]